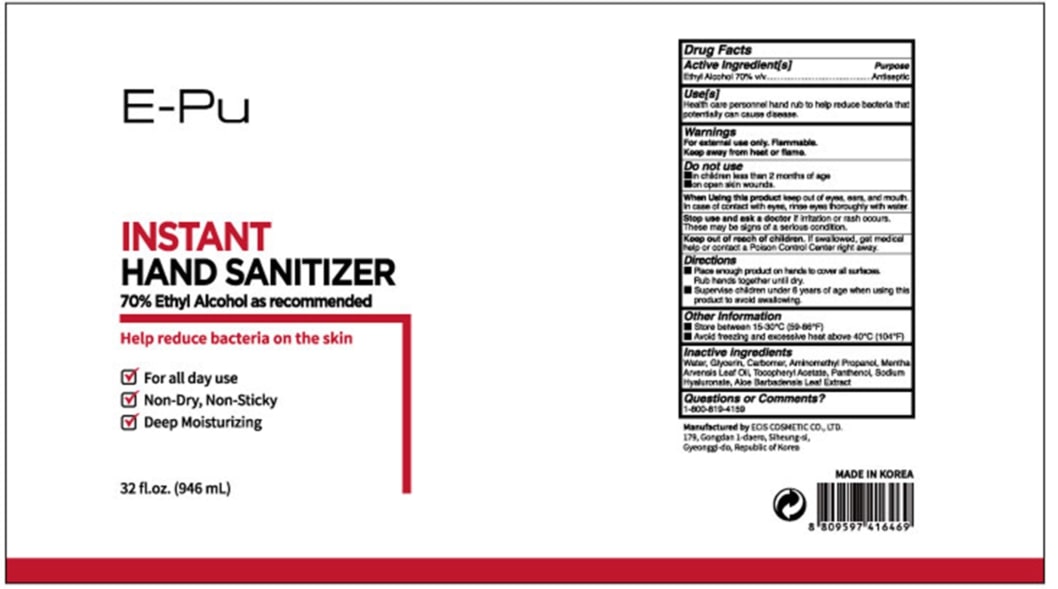 DRUG LABEL: EPU Hand Sanitizer 946ml
NDC: 73862-217 | Form: GEL
Manufacturer: E.CIS Cosmetic Co.,Ltd
Category: otc | Type: HUMAN OTC DRUG LABEL
Date: 20200617

ACTIVE INGREDIENTS: ALCOHOL 70 mL/100 mL
INACTIVE INGREDIENTS: AMINOMETHYLPROPANOL; MENTHA ARVENSIS LEAF OIL; PANTHENOL; GLYCERIN; CARBOMER 940; WATER; .ALPHA.-TOCOPHEROL ACETATE; ALOE VERA LEAF; HYALURONATE SODIUM

EPU Hand Sanitizer 946ml

Active Ingredient(s)

Alcohol 70% v/v. Purpose: Antiseptic

Purpose

Antiseptic, Hand Sanitizer

Use

Health care personnel hand rub to help reduce bacteria that potentially can cause disease.

Warnings

For external use only. Flammable. Keep away from heat or flame

Do not use

- in children less than 2 months of age
- on open skin wounds

When using this product keep out of eyes, ears, and mouth. In case of contact with eyes, rinse eyes thoroughly with water.

Stop use and ask a doctor if irritation or rash occurs. These may be signs of a serious condition.

Keep out of reach of children. If swallowed, get medical help or contact a Poison Control Center right away.

Directions

- Place enough product on hands to cover all surfaces. Rub hands together until dry.
- Supervise children under 6 years of age when using this product to avoid swallowing.

Other information

- Store between 15-30C (59-86F)
- Avoid freezing and excessive heat above 40C (104F)

Inactive ingredients

Water, Glycerin, Carbomer, Aminomethyl Propanol, Mentha Arvensis Leaf Oil, Tocopheryl Acetate, Panthenol, Sodium Hyaluronate,
Aloe Barbadensis Leaf Extract

Package Label - Principal Display Panel

EPU INSTANT HAND SANITIZER
70% Ethyl Alcohol as recommended
Help Reduce Bacteria On The Skin.
For all day use

Non-Day, Non-Sticky

Deep Moisturizing,
32 fl.oz (946ml)